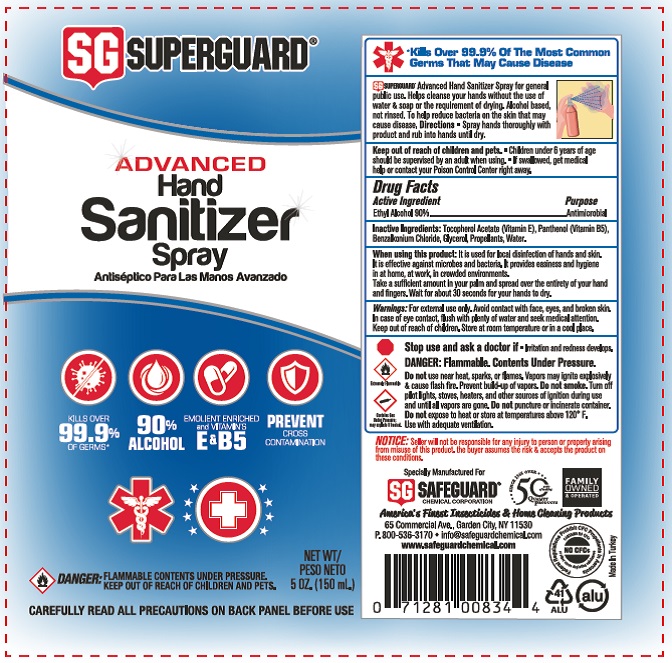 DRUG LABEL: SUPERGUARD Hand Sanitizer
NDC: 77462-001 | Form: AEROSOL
Manufacturer: SORA KOZMETIK SANAYI TICARET ANONIM SIRKETI
Category: otc | Type: HUMAN OTC DRUG LABEL
Date: 20200618

ACTIVE INGREDIENTS: ALCOHOL 90 mL/100 mL
INACTIVE INGREDIENTS: BENZALKONIUM CHLORIDE; PANTHENOL; WATER; GLYCERIN; ALPHA-TOCOPHEROL ACETATE

SUPERGUARD

Active Ingredient

Ethyl Alcohol 90%

Purpose

Antimicrobial

Use

It is used for local disinfection of hands and skin. It is effective against microbes and bacteria. It provides easiness and hygiene in at home, at work, in crowded environments.

Warnings

For external use only.

DANGER: Flammable. Contents Under Pressure.

Do not use near heat, sparks, or flames. Vapors may ignite explosively & cause flash fire. Prevent build-up of vapors. Do not smoke. Turn off pilot light, stoves, heaters, and other sources of ignition during use and until all vapors are gone. Do not puncture or incinerate container. Do not expose to heat or store at temperatures about 120F. Use with adequate ventilation.

Stop use and ask a doctor if irritation or redness develops.

WHEN USING

Avoid contact with face, eyes, and broken skin. In case of eye contact, flush with plenty of water and seek medical attention.

Keep out of reach of children.

Directions

Take a suffiicent amount in your palm and spread over the entirety of your hand and fingers. Wait for about 30 seconds for your hands to dry.

Other information

Store at room temperature or in a cool place.

Inactive ingredients

Tocopherol Acetate (Vitamin E), Panthenol (Vitamin B5), Benzalkonium Chloride, Glycerol, Propellants, Water.